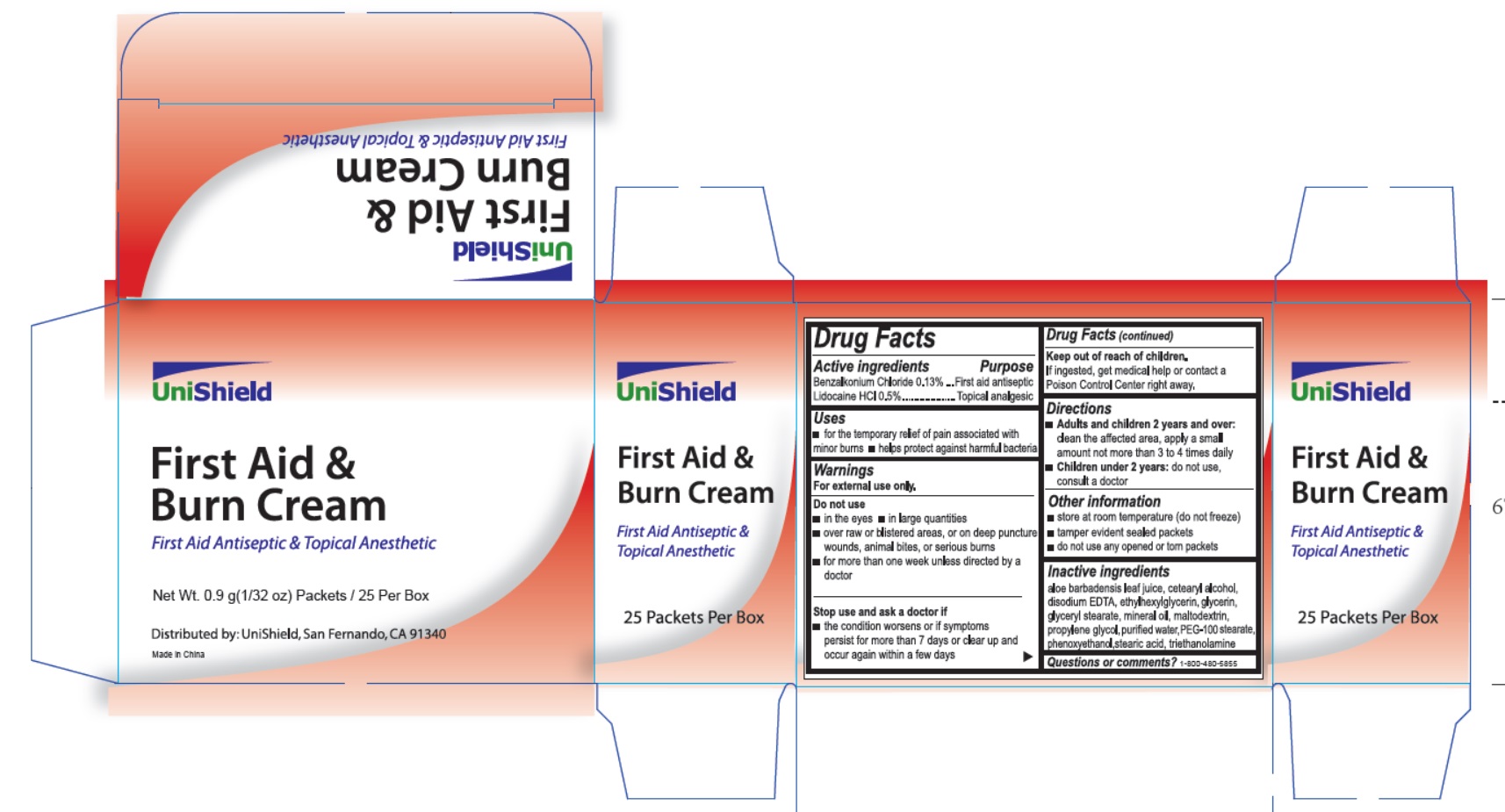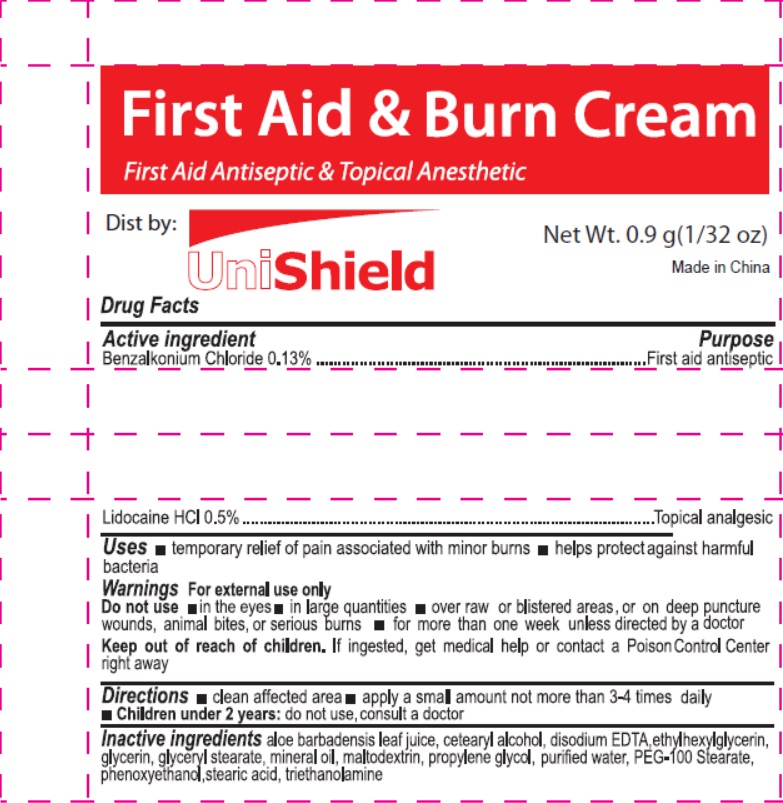 DRUG LABEL: FIRST SHIELD
NDC: 49314-0003 | Form: CREAM
Manufacturer: Unishield
Category: otc | Type: HUMAN OTC DRUG LABEL
Date: 20230403

ACTIVE INGREDIENTS: LIDOCAINE HYDROCHLORIDE 5 mg/1 g; BENZALKONIUM CHLORIDE 1.3 mg/1 g
INACTIVE INGREDIENTS: GLYCERYL MONOSTEARATE; MINERAL OIL; MALTODEXTRIN; PEG-100 STEARATE; STEARIC ACID; ETHYLHEXYLGLYCERIN; PHENOXYETHANOL; WATER; GLYCERIN; EDETATE DISODIUM ANHYDROUS; PROPYLENE GLYCOL; TROLAMINE; ALOE VERA LEAF; CETOSTEARYL ALCOHOL

Unishield First Aid & Burn Cream

Active ingredient

Benzalkonium Chloride 0.13%

Lidocaine HCl 0.5%

Purpose

First aid antiseptic

Topical analgesic

Uses

- temporary relief of pain associated with minor burns
- helps protect against harmful bacteria

Warnings

For external use only.

Do not use

- in eyes
- in large quantities
- over raw surfaces or blistered areas, or on deep puncture wounds, animal bites, serious burns
- for more than one week unless directed by a doctor

Keep out of reach of children.

If ingested, get medical help or contact a Poison Control Center right away.

Directions

- clean affected area
- apply a small amount not more than 3-4 times daily
- children under 2 years: do not use,consult a doctor

Other Information

- store at room temperature (do not freeze)
- tamper evident sealed packets
- do not use any opened or torn packets

Inactive ingredients

aloe barbadensis leaf juice, cetearyl alcohol, disodium EDTA,ethylhexylglycerin, glycerin, glyceryl stearate, mineral oil, maltodextrin, propylene glycol,purified water, PEG-100 Stearate, phenoxyethanol, stearic acid, triethanolamine

Questions or comments?

1-800-480-5855